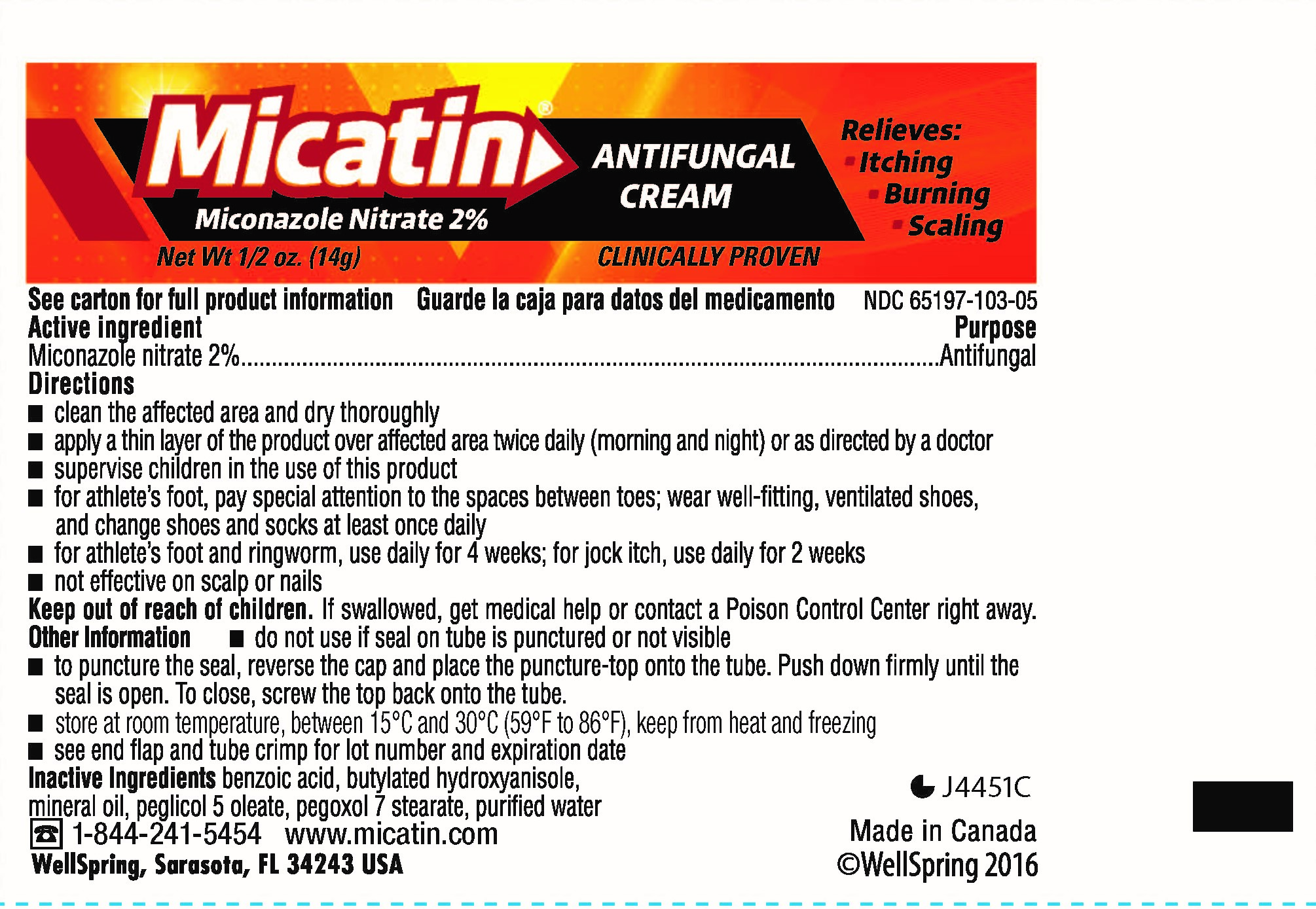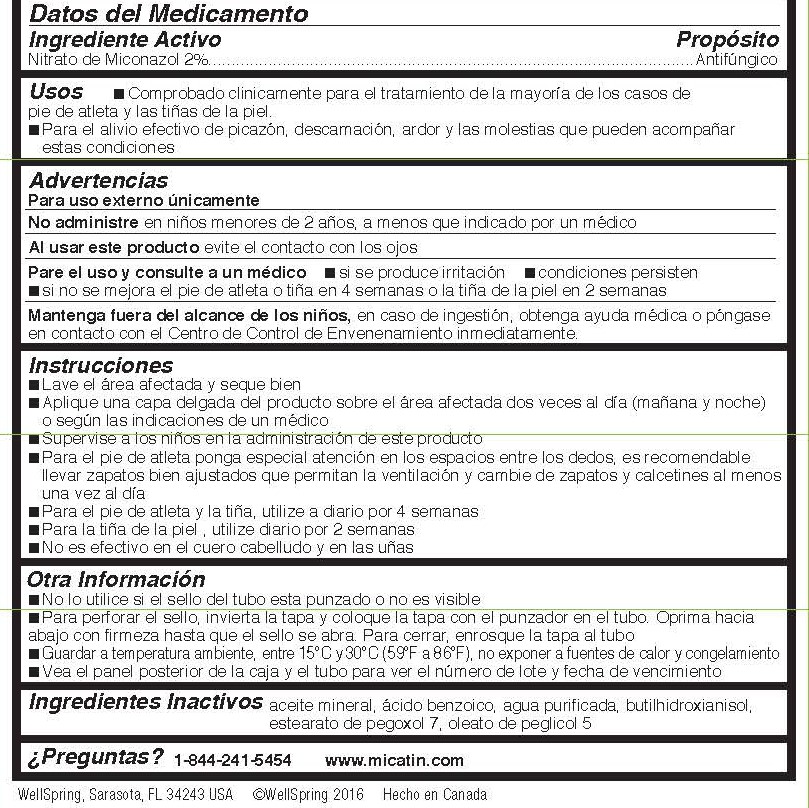 DRUG LABEL: Micatin
NDC: 65197-103 | Form: CREAM
Manufacturer: WellSpring Pharmaceutical Corporation
Category: otc | Type: HUMAN OTC DRUG LABEL
Date: 20160407

ACTIVE INGREDIENTS: MICONAZOLE NITRATE 20 mg/1 g
INACTIVE INGREDIENTS: BENZOIC ACID; BUTYLATED HYDROXYANISOLE; MINERAL OIL

Micatin

ACTIVE INGREDIENT/INGREDIENTE ACTIVO

Miconazole nitrate 2% / Nitrato de Miconazol 2%

PURPOSE/PROPÓSITO

Antifungal/Antifúngico

USES/USOS

- proven clinically effective in the treatment of most athlete's foot, jock itch and ringworm /
  comprobado clínicamente para el tratamiento de la mayoría de los casos de pie de atleta, la sarna deportiva y la tiña
- for effective relief of itching, scaling, burning and discomfort that can company these conditions /
  Para el alivio efectivo de picazón, descamación, ardor y las molestias que pueden acompañar estas condiciones

WARNINGS/ADVERTENCIAS

For external use only / Para uso externo únicamente

When using this product / Al usar este producto

avoid contact with the eyes / evite el contacto con los ojos

Stop use and ask a doctor if / Pare el uso y consulte a un médico

- irritation occurs / si se produce irritación
- condition persists / condiciones persisten
- there is no improvement of athlete's foot or ringworm within 4 weeks or jock itch within 2 weeks / si no se mejora el pie de atleta o tiña en 4 semanas o la sarna deportiva en 2 semanas

Keep out of reach of children. Mantenga fuera del alcance de los niños,

If swallowed, get medical help or contact a Poison Control Center right away. (1-800-222-1222) /
en caso de ingestión, obtenga ayuda médica o póngase en contacto con el Centro de Control de Envenenamiento inmediatamente.

DIRECTIONS/INSTRUCCIONES

- clean the affected area and dry thoroughly / Lave el área afectada y seque bien
- apply a thin layer of the product over affected area twice daily (morning and night) or as directed by a doctor /
  Aplique una capa delgada del producto sobre el área afectada dos veces al día (mañana y noche) o según las indicaciones de un médico
- supervise children in the use of this product / Supervise a los niños en la administración de este producto
- for athlete's foot, pay special attention to the spaces between the toes; wear well-fitting, ventilated shoes, and change shoes and socks at least once daily / Para el pie de atleta ponga especial atención en los espacios entre los dedos, es recomendable llevar zapatos bien ajustados que permitan la ventilación y cambie de zapatos y calcetines al menos una vez al día
- for athlete's foot and ringworm, use daily for 4 weeks / Para el pie de atleta y la tiña, utilice a diario por 4 semanas
- for jock itch, use daily for 2 weeks / Para la sarna deportiva, utilice a diario por 2 semanas
- not effective on the scalp or nails / No es efectivo en el cuero cabelludo y en las uñas

OTHER INFORMATION/OTRA INFORMACION

- do not use if seal on tube is punctured or not visible / No lo utilice si el sello del tubo esta punzado o no es visible
- to puncture the seal, reverse the cap and place the puncture-top onto the tube. Push down firmly until the seal is open. To close, screw the top back on the the tube. / Para perforar el sello, invierta la tapa y coloque la tapa con el punzador en el tubo. Oprima hacia abajo con firmeza hasta que el sello se abra. Para cerrar, enrosque la tapa al tubo
- store at 20º to 25ºC (68º to 77ºF) / Almacénelo de 20° a 25° C (68° a 77° F)
- see carton back panel and tube crimp for lot number and expiration date. / Vea el panel posterior de la caja y el tubo para ver el número de lote y fecha de vencimiento

INACTIVE INGREDIENTS/INGREDIENTES INACTIVOS

benzoic acid, butylated hydroxyanisole, mineral oil, peglicol 5 oleate, pegoxol 7 stearate, purified water /
aceite mineral, ácido benzoico, agua purificada, butilhidroxianisol, estearato de pegoxol 7, oleato de peglicol 5

QUESTIONS?/¿PREGUNTAS?

1-844-241-5454 www.micatin.com

DISTRIBUTED BY / DIST.

WellSpring Pharmaceutical Corporation
Sarasota, FL 34243 USA

© WellSpring 2016

Made in Canada / Hecho en Canada